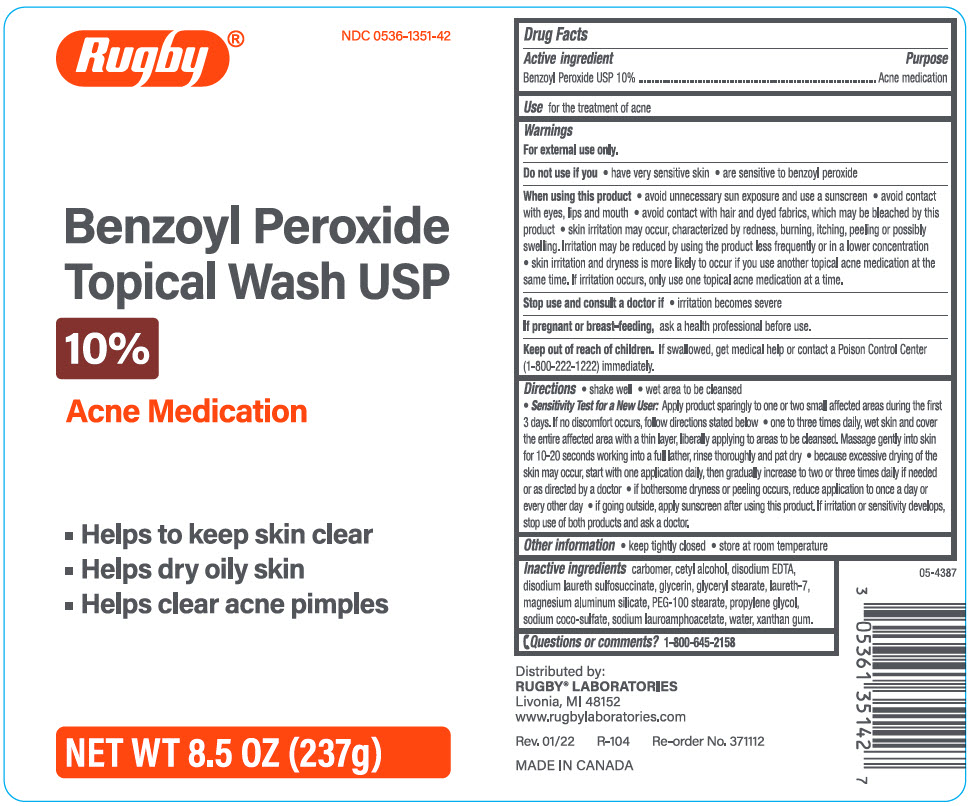 DRUG LABEL: Rugby Benzoyl Peroxide Wash
NDC: 0536-1351 | Form: LOTION
Manufacturer: Rugby Laboratories
Category: otc | Type: HUMAN OTC DRUG LABEL
Date: 20240301

ACTIVE INGREDIENTS: Benzoyl Peroxide 100 mg/1 g
INACTIVE INGREDIENTS: CARBOMER HOMOPOLYMER, UNSPECIFIED TYPE; Cetyl Alcohol; EDETATE DISODIUM; Disodium Laureth Sulfosuccinate; Glycerin; GLYCERYL MONOSTEARATE; Laureth-7; Magnesium Aluminum Silicate; PEG-100 Stearate; Propylene Glycol; Sodium Coco-Sulfate; Sodium Lauroamphoacetate; Water; Xanthan Gum

Rugby® 10% Benzoyl Peroxide Wash USP

Drug Facts

Active ingredient

Benzoyl peroxide USP 10%

Purpose

Acne medication

Use

for the treatment of acne

Warnings

For external use only.

Do not use if you

- have very sensitive
- are sensitive to benzoyl peroxide

When using this product

- avoid unnecessary sun exposure and use a sunscreen
- avoid contact with eyes, lips and mouth
- avoid contact with hair or dyed fabrics, which may be bleached by this product
- skin irritation may occur, characterized by redness, burning, itching, peeling, or possibly swelling. Irritation may be reduced by using the product less frequently or in a lower concentration.
- skin irritation and dryness is more likely to occur if you use another topical acne medication at the same time. If irritation occurs, only use one topical acne medication at a time.

Stop use and consult a doctor if

- irritation becomes severe

PREGNANCY OR BREAST FEEDING

If pregnant or breast-feeding, ask a health professional before use.

Keep out of reach of children. If swallowed, get medical help or contact a Poison Control Center (1-800-222-1222) immediately.

Directions

- shake well
- Wet area to be cleansed
- Sensitive Test for a New User. Apply product sparingly to one or two small affected areas during the first 3 days. If no discomfort occurs, follow directions stated below
- one to three times daily, wet skin and cover the entire affected area with a thin layer, liberally applying to areas to be cleansed. Massage gently into skin for 10-20 seconds working into a full lather, rinse thoroughly and pat dry
- because excessive drying of the skin may occur, start with one application daily, then gradually increase to two or three times daily if needed or as directed by a doctor
- if bothersome dryness or peeling occurs, reduce application to once a day or every other day
- if going outside, apply sunscreen after using this product. If irritation or sensitivity develops, stop use of both products and ask a doctor.

Other information

- keep tightly closed
- store at room temperature

Inactive ingredients

carbomer, cetyl alcohol, disodium EDTA, disodium laureth sulfosuccinate, glycerin, glyceryl stearate, laureth-7, magnesium aluminum silicate, PEG-100 stearate, propylene glycol, sodium coco-sulfate, sodium lauroamphoacetate, water, xanthan gum.

Questions or comments?

1-800-645-2158

Distributed by:
RUGBY® LABORATORIES
Livonia, MI 48152

PRINCIPAL DISPLAY PANEL - 237 g Bottle Label

Rugby®

NDC 0536-1351-42

Benzoyl Peroxide
Topical Wash USP

10%

Acne Medication

- Helps to keep skin clear
- Helps dry oily skin
- Helps clear acne pimples

NET WT 8.5 OZ (237g)